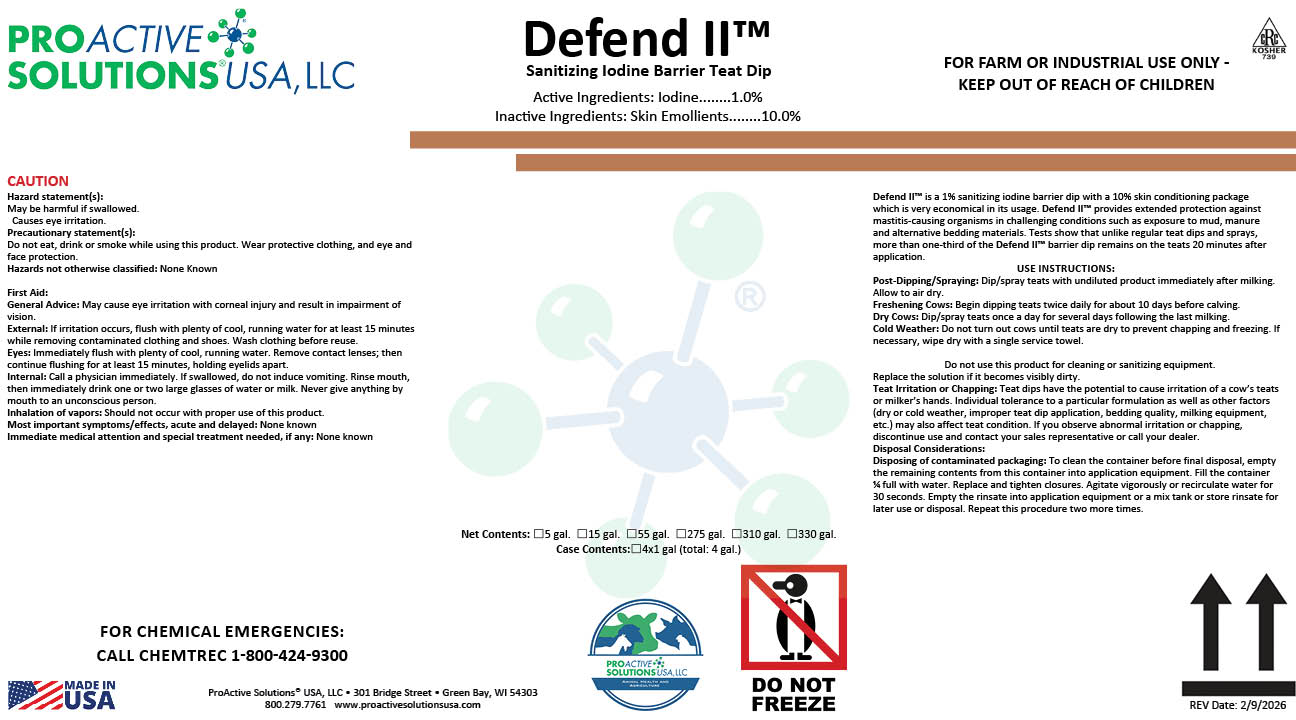 DRUG LABEL: Defend II
NDC: 63927-4121 | Form: LIQUID
Manufacturer: ProActive Solutions USA, LLC
Category: animal | Type: OTC ANIMAL DRUG LABEL
Date: 20260210

ACTIVE INGREDIENTS: IODINE 1 kg/100 kg

Defend II

Defend II

Defend II™ is a 1% sanitizing iodine barrier dip with a 10% skin conditioning package
which is very economical in its usage. Defend II™ provides extended protection against
mastitis-causing organisms in challenging conditions such as exposure to mud, manure
and alternative bedding materials. Tests show that unlike regular teat dips and sprays,
more than one-third of the Defend II™ barrier dip remains on the teats 20 minutes after
application.
USE INSTRUCTIONS:
Post-Dipping/Spraying: Dip/spray teats with undiluted product immediately after milking.
Allow to air dry.
Freshening Cows: Begin dipping teats twice daily for about 10 days before calving.
Dry Cows: Dip/spray teats once a day for several days following the last milking.
Cold Weather: Do not turn out cows until teats are dry to prevent chapping and freezing. If
necessary, wipe dry with a single service towel.
Do not use this product for cleaning or sanitizing equipment.
Replace the solution if it becomes visibly dirty.
Teat Irritation or Chapping: Teat dips have the potential to cause irritation of a cow’s teats
or milker’s hands. Individual tolerance to a particular formulation as well as other factors
(dry or cold weather, improper teat dip application, bedding quality, milking equipment,
etc.) may also affect teat condition. If you observe abnormal irritation or chapping,
discontinue use and contact your sales representative or call your dealer.
Disposal Considerations:
Disposing of contaminated packaging: To clean the container before final disposal, empty
the remaining contents from this container into application equipment. Fill the container
¼ full with water. Replace and tighten closures. Agitate vigorously or recirculate water for
30 seconds. Empty the rinsate into application equipment or a mix tank or store rinsate for
later use or disposal. Repeat this procedure two more times.

Hazard statement(s):
May be harmful if swallowed.
Causes eye irritation.
Precautionary statement(s):
Do not eat, drink or smoke while using this product. Wear protective clothing, and eye and
face protection.
Hazards not otherwise classified: None Known
First Aid:
General Advice: May cause eye irritation with corneal injury and result in impairment of
vision.
External: If irritation occurs, flush with plenty of cool, running water for at least 15 minutes
while removing contaminated clothing and shoes. Wash clothing before reuse.
Eyes: Immediately flush with plenty of cool, running water. Remove contact lenses; then
continue flushing for at least 15 minutes, holding eyelids apart.
Internal: Call a physician immediately. If swallowed, do not induce vomiting. Rinse mouth,
then immediately drink one or two large glasses of water or milk. Never give anything by
mouth to an unconscious person.
Inhalation of vapors: Should not occur with proper use of this product.
Most important symptoms/effects, acute and delayed: None known
Immediate medical attention and special treatment needed, if any: None known